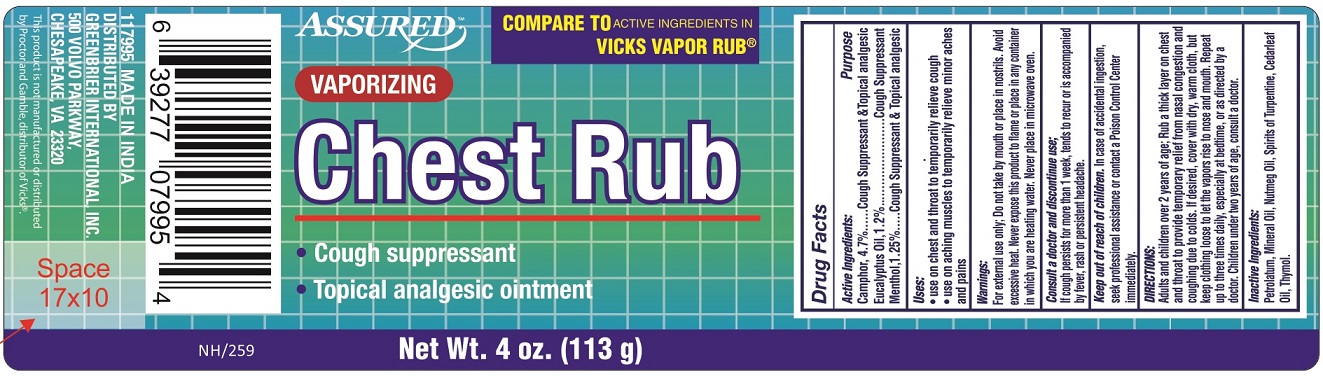 DRUG LABEL: Assured Vaporizing Chest Rub
NDC: 33992-7992 | Form: OINTMENT
Manufacturer: Greenbrier International, Inc.
Category: otc | Type: HUMAN OTC DRUG LABEL
Date: 20190119

ACTIVE INGREDIENTS: CAMPHOR (SYNTHETIC) 4.7 g/100 g; EUCALYPTUS OIL 1.2 g/100 g; MENTHOL 1.25 g/100 g
INACTIVE INGREDIENTS: PETROLATUM; MINERAL OIL; NUTMEG OIL; TURPENTINE OIL; CEDAR LEAF OIL; THYMOL

Active Ingredients

Camphor 4.7%

Eucalyptus Oil 1.2%

Menthol 1.25%

Purpose

Cough Suppressant & Topical analgesic

Cough Suppressant

Cough Suppressant & Topical analgesic

Uses

- use on chest and throat to temporarily relieve cough
- use on aching muscles to temporarily relieve minor aches and pains

Warnings

For external use only; Do not take by mouth or place in nostrils. Avoid excessive heat. Never expose this product to flame or place in any container in which you are heating water. Never place in microwave oven.

Consult a doctor and discontinue use;

If cough persist for more than 1 week, tends to recur or is accompanied by fever, rash or persistent headache.

Keep out of reach of children

In case of accidental ingestion, seek professional assistance or contact a Poison Control Centre immediately.

Directions:

- Adults and children over 2 years of age; Rub a thick layer on chest and throat to provide temporary relief from nasal congestion and coughing due to colds. If desired, cover with dry, warm cloth, but keep clothing loose to let the vapours rise to nose and mouth. Repeat up to three times daily, especially at bedtime, or as directed by a doctor.
- Children under two years of age, consult a doctor.

Inactive Ingredients:

Petrolatum, Mineral Oil, Nutmeg Oil, Spirits of Turpentine, Cedarleaf Oil, Thymol

PACKAGE LABEL

PRINCIPAL DISPLAY PANEL

ASSURED VAPORIZING CHEST RUB